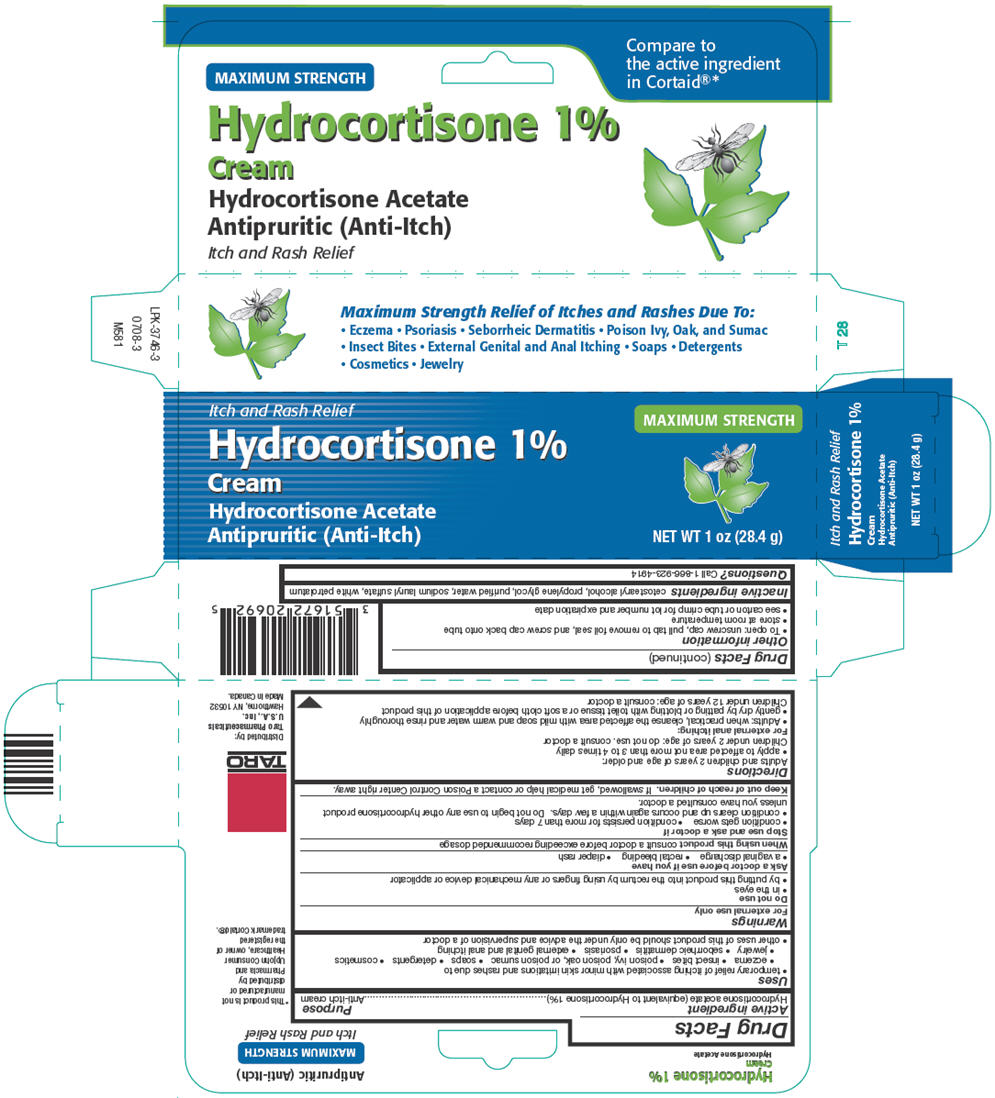 DRUG LABEL: Hydrocortisone Acetate 

NDC: 51672-2069 | Form: CREAM
Manufacturer: Sun Pharmaceutical Industries, Inc.
Category: otc | Type: HUMAN OTC DRUG LABEL
Date: 20251202

ACTIVE INGREDIENTS: HYDROCORTISONE ACETATE 1 g/100 g
INACTIVE INGREDIENTS: CETOSTEARYL ALCOHOL; PROPYLENE GLYCOL; WATER; SODIUM LAURYL SULFATE; PETROLATUM

Hydrocortisone 1% Cream

Drug Facts

Active ingredient

Hydrocortisone acetate (equivalent to Hydrocortisone 1%)

Purpose

Anti-itch cream

Uses

- temporary relief of itching associated with minor skin irritations and rashes due to
  - eczema
  - insect bites
  - poison ivy, poison oak, or poison sumac
  - soaps
  - detergents
  - cosmetics
  - jewelry
  - seborrheic dermatitis
  - psoriasis
  - external genital and anal itching
- other uses of this product should be only under the advice and supervision of a doctor

Warnings

For external use only

Do not use

- in the eyes
- by putting this product into the rectum by using fingers or any mechanical device or applicator

Ask a doctor before use if you have

- a vaginal discharge
- rectal bleeding
- diaper rash

WHEN USING

When using this productconsult a doctor before exceeding recommended dosage

Stop use and ask a doctor if

- condition gets worse
- condition persists for more than 7 days
- condition clears up and occurs again within a few days. Do not begin to use any other hydrocortisone product unless you have consulted a doctor.

Keep out of reach of children.If swallowed, get medical help or contact a Poison Control Center right away.

Directions

Adults and children 2 years of age and older:

- apply to affected area not more than 3 to 4 times daily

Children under 2 years of age: do not use. consult a doctor

For external anal itching:

- Adults: when practical, cleanse the affected area with mild soap and warm water and rinse thoroughly
- gently dry by patting or blotting with toilet tissue or a soft cloth before application of this product

Children under 12 years of age: consult a doctor

Other information

- To open: unscrew cap, pull tab to remove foil seal, and screw cap back onto tube
- store at room temperature
- see carton or tube crimp for lot number and expiration date

Inactive ingredients

cetostearyl alcohol, propylene glycol, purified water, sodium lauryl sulfate, white petrolatum

Questions?

Call 1-866-923-4914

Distributed by:
Taro Pharmaceuticals
U.S.A., Inc.
Hawthorne, NY 10532

PRINCIPAL DISPLAY PANEL - 28.4 g Carton

Itch and Rash Relief

Hydrocortisone 1%
Cream
Hydrocortisone Acetate
Antipruritic (Anti-Itch)

MAXIMUM STRENGTH

NET WT 1 oz (28.4 g)